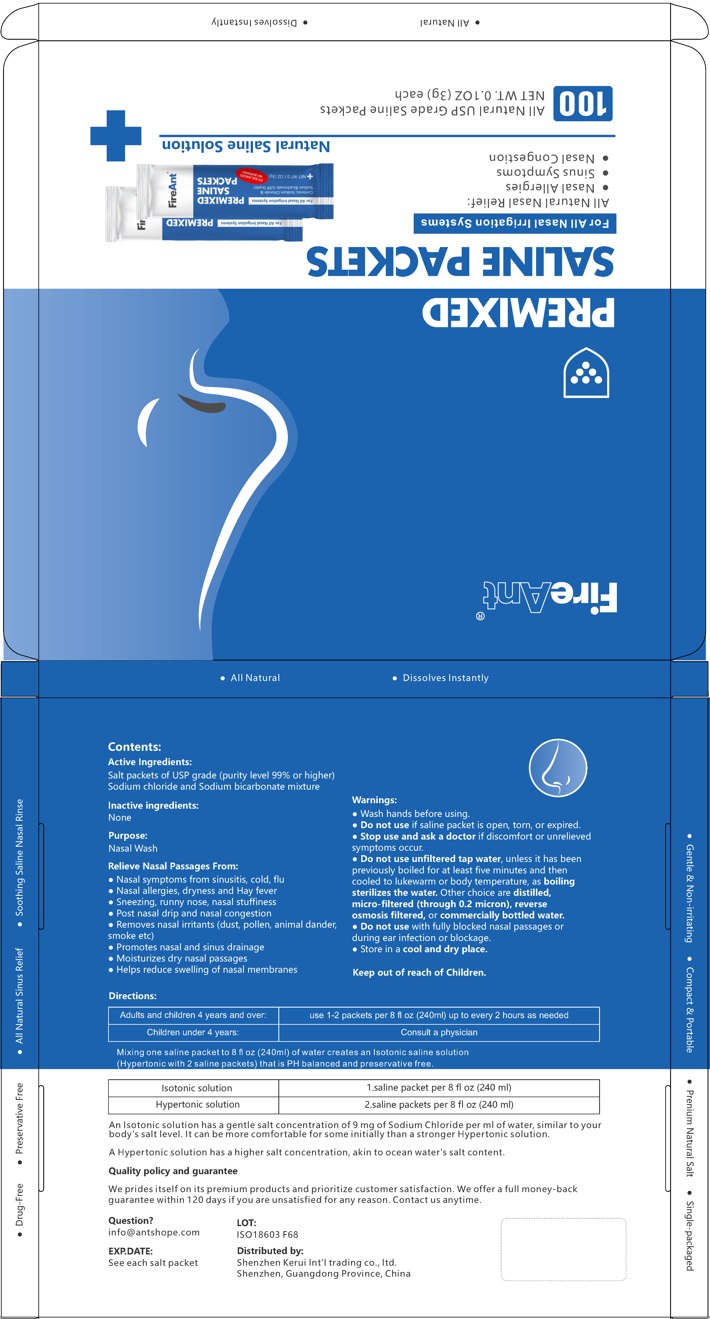 DRUG LABEL: Premixed saline packets
NDC: 83879-001 | Form: GRANULE, FOR SOLUTION
Manufacturer: Shenzhen Kerui lnt’l Trading Co., Ltd
Category: otc | Type: HUMAN OTC DRUG LABEL
Date: 20250109

ACTIVE INGREDIENTS: SODIUM BICARBONATE 700 mg/3000 mg; SODIUM CHLORIDE 2300 mg/3000 mg

83879-001-01

Active ingredient

Sodium Chloride USP 2300mg

Sodium Bicarbonate USP 700mg

Purpose

Nasal Wash

Uses

Relieve Nasal Passages From:

■Nasal symptoms from sinusitis, cold, flu ■Nasal allergies, dryness and Hay fever ■Sneezing, runny nose, nasal stuffiness

■lPost nasal drip and nasal congestion ■Removes nasal irritants (dust, pollen, animal dander, smoke etc)

■Promotes nasal and sinus drainage l■Moisturizes dry nasal passages ■Helps reduce swelling of nasal membranes

Warnings

Do not use

■ if saline packet is open, torn, or expired.

■ with fully blocked nasal passages or during ear infection or blockage.

■ unfiltered tap water, unless it has been previously boiled for at least five minutes and then cooled to lukewarm or body temperature, as boiling sterilizes the water. Other choice are distilled, micro-filtered (through 0.2 micron), reverse osmosis filtered, or commercially bottled water.

When using this product

Wash hands before using

Stop use and ask a doctor

if discomfort or unrelieved symptoms occur.

Directions

Adults and children 4 years and over: | use 1-2 packets per 8 fl oz (240ml) up to every 2 hours as needed
Children under 4 years: | Consult a physician
Mixing one saline packet to 8 fl oz (240ml) of water creates an Isotonic saline solution (Hypertonic with 2 saline packets) that is PH balanced and preservative free.
Isotonic solution | 1 saline packet per 8 fl oz (240 ml)
Hypertonic solution | 2 saline packets per 8 fl oz (240 ml)
An Isotonic solution has a gentle salt concentration of 9 mg of Sodium Chloride per ml of water, similar to your body's salt level. It can be more comfortable for some initially than a stronger Hypertonic solution.
A Hypertonic solution has a higher salt concentration, akin to ocean water's salt content.

Other information

Store in a cool and dry place.

Inactive ingredients

None